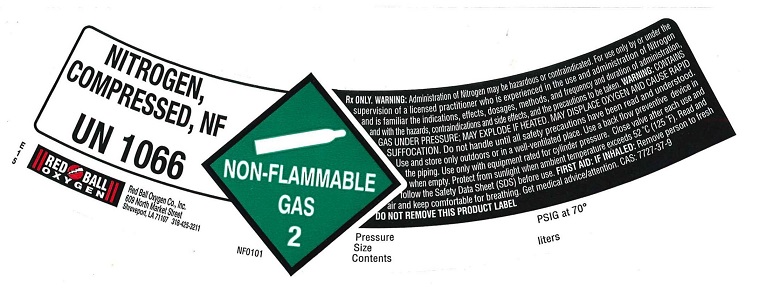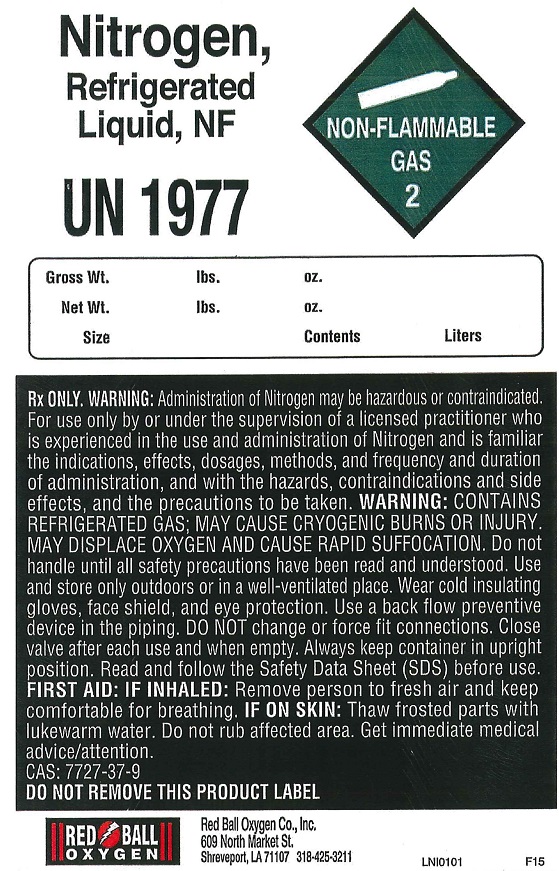 DRUG LABEL: Nitrogen
NDC: 46362-012 | Form: GAS
Manufacturer: Red Ball Oxygen Co., Inc.
Category: animal | Type: PRESCRIPTION ANIMAL DRUG LABEL
Date: 20251118

ACTIVE INGREDIENTS: Nitrogen 992 mL/1 L

nitrogen

PACKAGE LABEL

NITROGEN, COMPRESSED NF UN1066 NON-FLAMMABLE GAS 2
Rx only. WARNING: Administration of Nitrogen may be hazardous or contraindicated. For use only by or under the supervision of a licensed practitioner who is experienced in the use and administration of Nitrogen and is familiar with the indications, effects, dosages, methods, and frequency and duration of administration, and with the hazards, contraindications, and side effects and the precautions to be taken. WARNING: CONTAINS GAS UNDER PRESSURE; MAY EXPLODE IF HEATED. MAY DISPLACE OXYGEN AND CAUSE RAPID SUFFOCATION. Do not handle until all safety precautions have been read and understood. Use and store only outdoors or in a well-ventilated place. Use a back flow preventive device in the piping. Use only with equipment rated for cylinder pressure. Close valve after each use and when empty. Protect from sunlight when ambient temperature exceeds 52 degrees C (125 degrees F). Read and follow the Safety Data Sheet (SDS) before use. FIRST AID: IF INHALED: Remove person to fresh air and keep comfortable for breathing. Get medical advice/attention.
CAS: 7727-37-9 DO NOT REMOVE THIS PRODUCT LABEL Pressure Size Contents PSIG at 70 degrees liters
RED BALL OXYGEN
Red Ball Oxygen CO., Inc. 609 North Market Street Shreveport, LA 71107 318-425-3211

PACKAGE LABEL

NITROGEN, REFRIGERATED LIQUID, NF UN1977 NON-FLAMMABLE GAS 2
Gross Wt. lbs. oz. Net Wt. lbs. oz. Size Contents Liters
Rx ONLY. WARNING: Administration of Nitrogen may be hazardous or contraindicated. For use only by or under the supervision of a licensed practitioner who is experienced in the use and administration of Nitrogen and is familiar with the indications, effects, dosages, methods, and frequency and duration of administration, and with the hazards, contraindications, and side effects and the precautions to be taken. WARNING: CONTAINS REFRIGERATED GAS; MAY CAUSE CRYOGENIC BURNS OR INJURY. MAY DISPLACE OXYGEN AND CAUSE RAPID SUFFOCATION. Do not handle until all safety precautions have been read and understood. Use and store only outdoors or in a well-ventilated place. Wear cold insulating gloves, face shield, and eye protection. Use a back flow preventive device in the piping. DO NOT change or force fit connections. Close valve after each use and when empty. Always keep container in upright position. Read and follow the Safety Data Sheet (SDS) before use. FIRST AID: IF INHALED: Remove person to fresh air and keep comfortable for breathing. IF ON SKIN: Thaw frosted parts with lukewarm water. Do not rub affected area. Get immediate medical advice/attention.
CAS: 7727-37-9 DO NOT REMOVE THIS PRODUCT LABEL Pressure Size Contents PSIG at 70 degrees liters
RED BALL OXYGEN
Red Ball Oxygen CO., Inc. 609 North Market Street Shreveport, LA 71107 318-425-3211